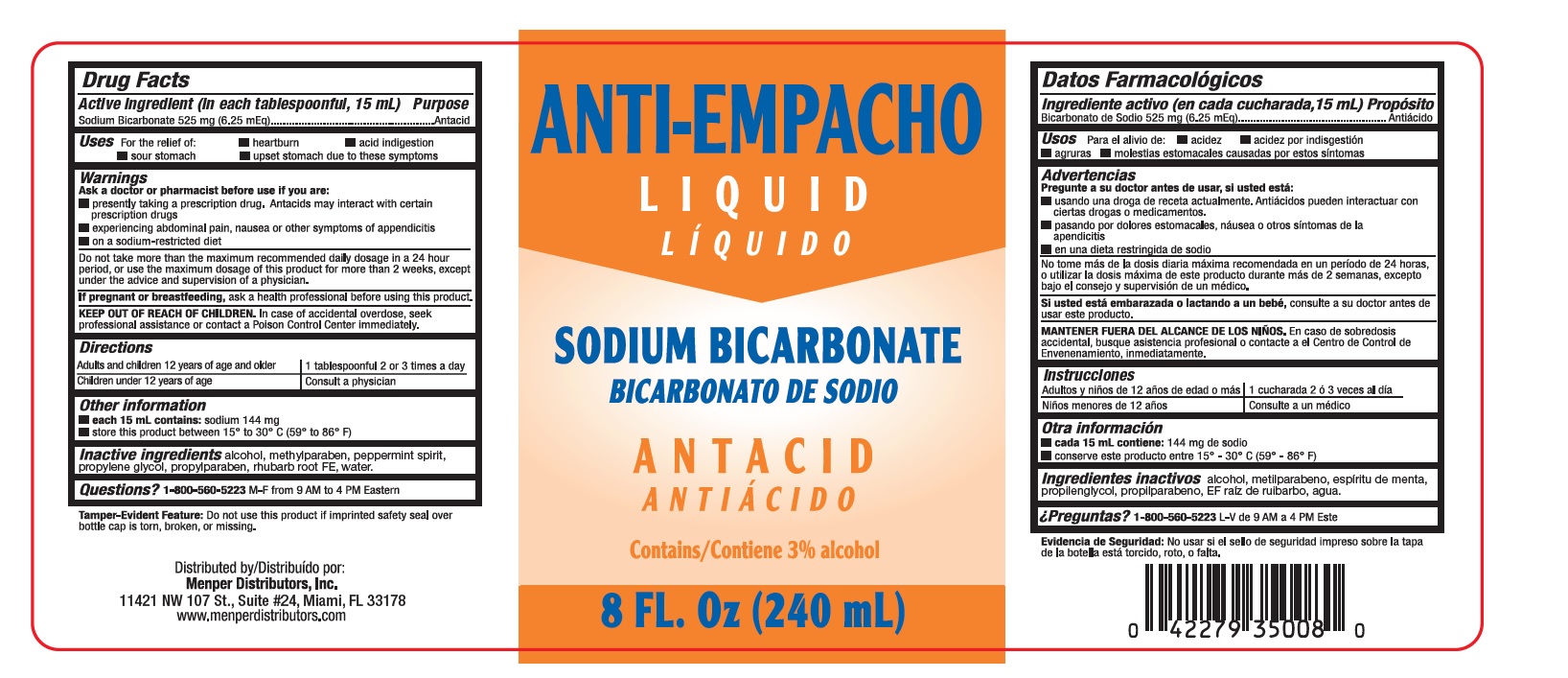 DRUG LABEL: Anti-Empacho
NDC: 53145-300 | Form: LIQUID
Manufacturer: Menper Distributors, Inc.
Category: otc | Type: HUMAN OTC DRUG LABEL
Date: 20250722

ACTIVE INGREDIENTS: SODIUM BICARBONATE 525 mg/15 mL
INACTIVE INGREDIENTS: ALCOHOL; METHYLPARABEN; PEPPERMINT; PROPYLENE GLYCOL; PROPYLPARABEN; RHUBARB; WATER

Anti-Empacho

Drug Facts

Active Ingredient (In each tablespoonful 15ml)

Sodium Bicarbonate 525 mg. (6.25 mEq)

Purpose

Antacid

Uses

For The relieve of:

- heartburn
- acid indigestion
- sour stomach
- upset stomach due to these symptoms

Ask a doctor or pharmacist before using if you are

- presently taking a prescription drug .Antacids may interact with certain prescription drugs
- experiencing abdominal pain, nausea or other symptoms of appendicitis
- on a sodium-restricted diet

WARNINGS

Do not take more than the maximum recomended daily dosage in a 24 hour period, or use the maximum dosage of this product for more than 2 weeks, except under the advice and supervision of a physician.

If pregnant or breastfeeding,

ask a health professional before using this product.

Keep out reach of children.

In case of accidental overdose, seek professional assistance or contact a Poison Control Center immediatly.

Directions

Adults and children 12 years of age and older ...................................1 tablespoonful 2 or 3 times a day

Children under 12 years of age .........................................................Consult a physician

Other information

- each 15 mL contains =: sodium 144 mg
- store this product between 15° to 30° C (59° to 86° F)

Inactive Ingredients

alcohol, methylparaben, peppermint spirit, propylene glycol, propylparaben, rhubarb FE, water

Questions?

1-800-560-5223 M-F from 9 AM to 4 PM Eastern